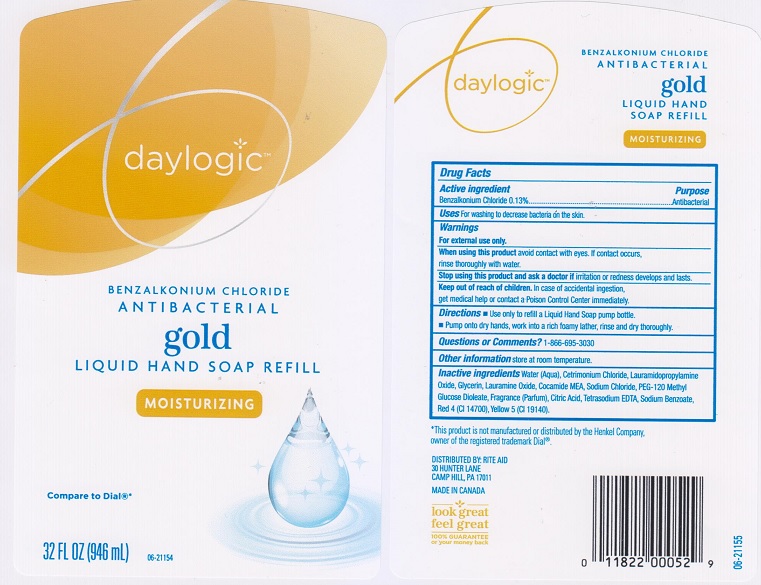 DRUG LABEL: Daylogic Antibacterial Gold Refill
NDC: 11822-2953 | Form: LIQUID
Manufacturer: Rite Aid Corporation
Category: otc | Type: HUMAN OTC DRUG LABEL
Date: 20161006

ACTIVE INGREDIENTS: BENZALKONIUM CHLORIDE 1.3 mg/1 mL
INACTIVE INGREDIENTS: WATER; CETRIMONIUM CHLORIDE; LAURAMIDOPROPYLAMINE OXIDE; GLYCERIN; LAURAMINE OXIDE; COCO MONOETHANOLAMIDE; SODIUM CHLORIDE; PEG-120 METHYL GLUCOSE DIOLEATE; CITRIC ACID MONOHYDRATE; EDETATE SODIUM; SODIUM BENZOATE; FD&C RED NO. 4; FD&C YELLOW NO. 5

Active ingredient

Benzalkonium chloride 0.13%

Purpose

Antibacterial

Uses

for washing to decrease bacteria on the skin.

Warnings

For external use only

When using this product

avoid contact with eyes. If contact occurs, rinse thoroughly with water.

Stop using this product and ask a doctor if

irritation or redness develops and lasts.

Keep out of reach of children.

In case of accidental ingestion, get medical help or contact a Poison Control Center immediately.

Directions

- use only to refill a Liquid Hand Soap pump bottle.
- Pump onto dry hands, work into a rich foamy lather, rinse and dry thoroughly.

Questions or Comments?

1-866-695-3030

Other information

store at room temperature

Inactive ingredients

Water (Aqua), Cetrimonium Chloride, Lauramidopropylamine Oxide, Glycerin, Lauramine Oxide, Cocamide MEA, Sodium Chloride, PEG-120 Methyl Glucose Dioleate, Fragrance (Parfum), Citric Acid, Tetrasodium EDTA, Sodium Benzoate, Red 4 (CI 14700), Yellow 5 (CI 19140).